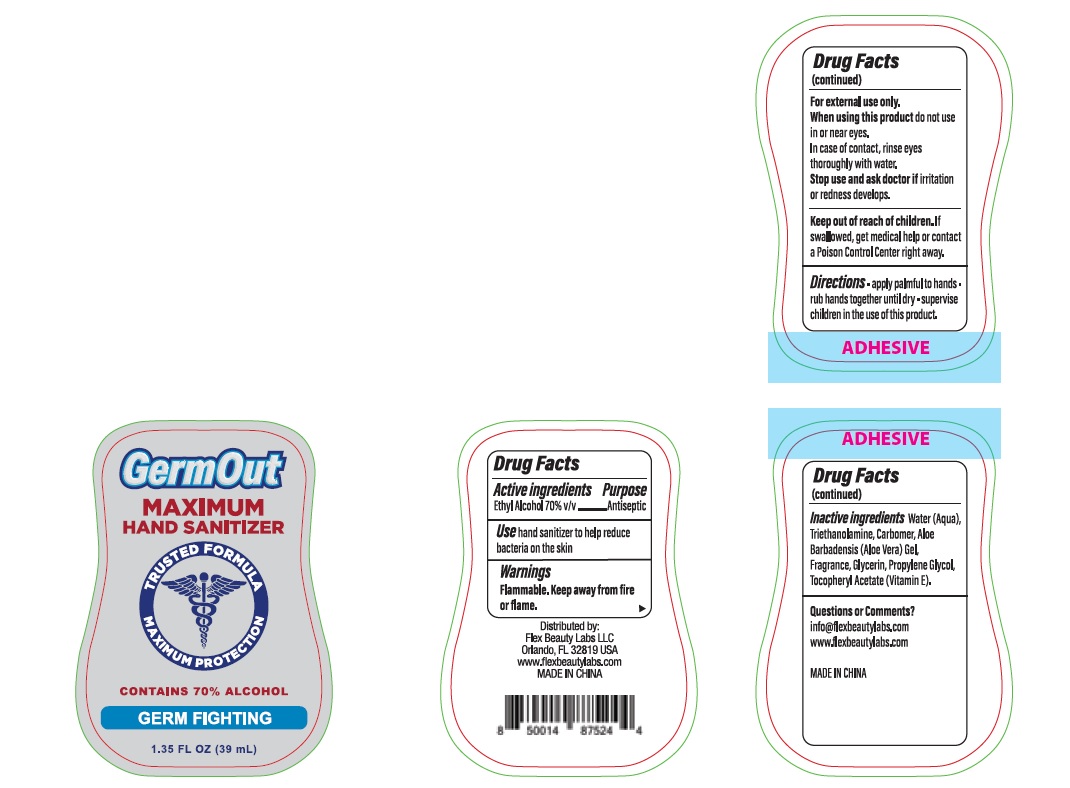 DRUG LABEL: Germ Out Hand Sanitizer
NDC: 72308-027 | Form: GEL
Manufacturer: Flex Beauty Labs
Category: otc | Type: HUMAN OTC DRUG LABEL
Date: 20200804

ACTIVE INGREDIENTS: ALCOHOL 0.7 mL/1 mL
INACTIVE INGREDIENTS: WATER; TROLAMINE; CARBOMER HOMOPOLYMER, UNSPECIFIED TYPE; PROPYLENE GLYCOL; GLYCERIN; ALOE VERA LEAF; ALPHA-TOCOPHEROL

Germ Out Hand Sanitizer

Active Ingredients

Ethyl Alcohol 70%.................Antiseptic

Purpose

Antiseptic

Use

hand sanitizer to help reduce bacteria on the skin

Safety Instructions

Flammable, Keep away from fire and flame

When using this product

In case of contact,rinse eyes thoroughly with water.

Do not use in or near eyes.

KEEP OUT OF REACH OF CHILDREN

If swallowed, get medical help or contact Poison Control center right away.

Inactive Ingredients

Water (aqua), Triethanolamine, Carbomer, Fragrance, Glycerin. Propylene Glycol, Aloe vera Gel, Tocopheyl Acetate.

Directions

- apply palmful to hands.
- rub hands together vigorously until dry.
- supervise children in the use of this product.